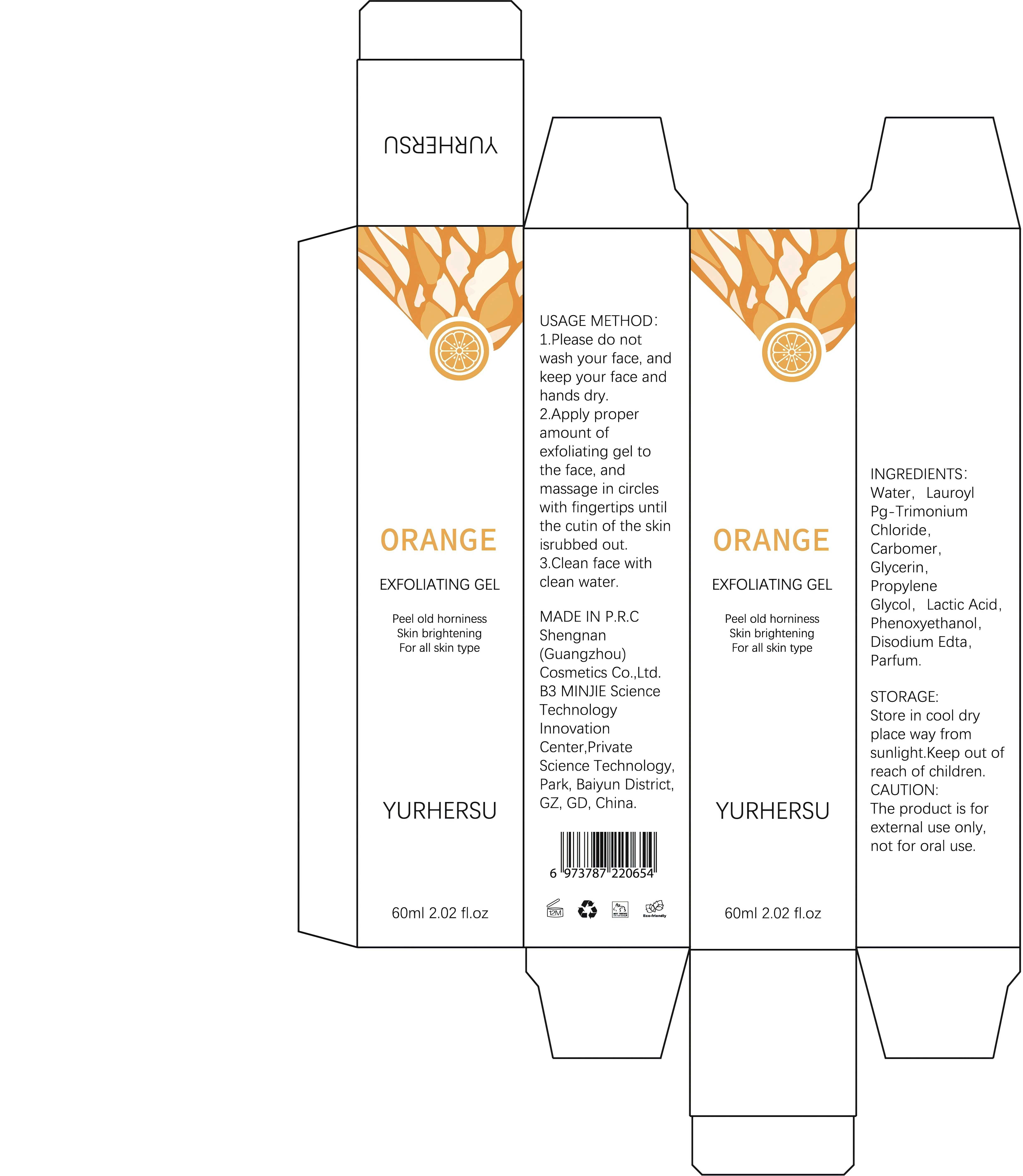 DRUG LABEL: ExfoliatingGel
NDC: 84019-020 | Form: CREAM
Manufacturer: Shengnan (Guangzhou) Cosmetics Co., Ltd
Category: otc | Type: HUMAN OTC DRUG LABEL
Date: 20241226

ACTIVE INGREDIENTS: LACTIC ACID 100 mg/1 mL
INACTIVE INGREDIENTS: GLYCERIN; PHENOXYETHANOL; LAUROYL PG-TRIMONIUM CHLORIDE; CARBOMER

EXFOLIATING GEL 60g

WARNINGS

Please keep out of reach of children.

PURPOSE

EXFOLIATING

STOP USE

Discontinueuse if signs of irritation or rash occur

ACTIVE INGREDIENT

Lactic Acid

WHEN USING

Please clean your hands before use to ensure the best results fromthe product.

INACTIVE INGREDIENT

Water

Lauroyl PG-Trimonium Chloride

Glycerin

Propylene Glycol

Phenoxyethanol

Carbomer

Disodium EDTA

Fragrance

DOSAGE AND ADMINISTRATION

Apply 1 times a day

INDICATIONS AND USAGE

1.Please do not wash your face, and keep your face and hands dry.2.Apply proper amount of exfoliating gel tothe face, and massage in circles with fingertips until the cutin of the skin is rubbed out.3.Clean face with clean water.